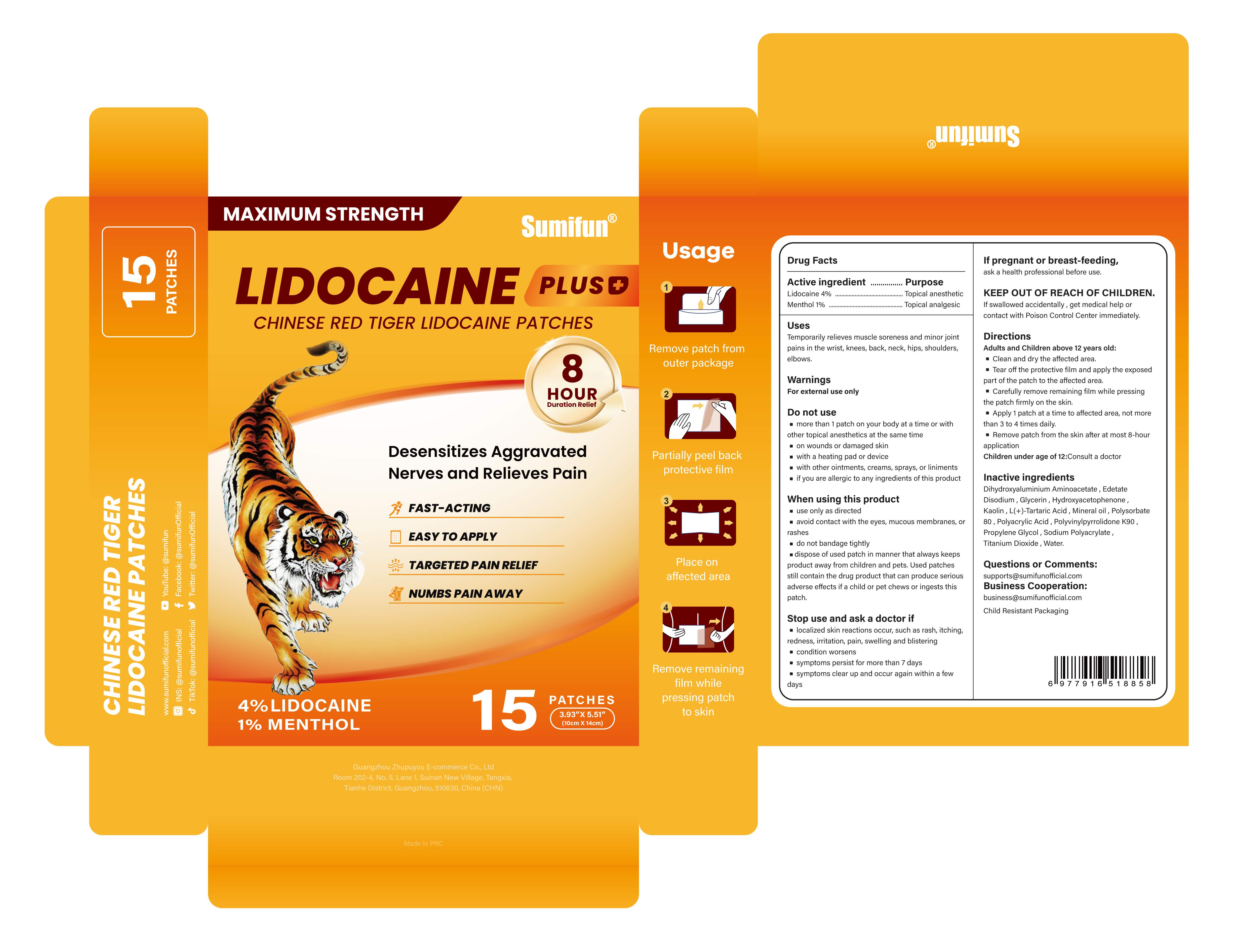 DRUG LABEL: CHINESE RED TIGER LIDOCAINE PATCHES
NDC: 84165-010 | Form: PATCH
Manufacturer: Guangzhou Zhupuyou E-commerce Co., Ltd
Category: otc | Type: HUMAN OTC DRUG LABEL
Date: 20250612

ACTIVE INGREDIENTS: LIDOCAINE 0.04 g/1 g; MENTHOL 0.01 g/1 g
INACTIVE INGREDIENTS: SODIUM POLYACRYLATE (2500000 MW); TARTARIC ACID; PROPYLENE GLYCOL; DIHYDROXYALUMINUM AMINOACETATE ANHYDROUS; POLYACRYLIC ACID (250000 MW); TITANIUM DIOXIDE; WATER; MINERAL OIL; EDETATE DISODIUM; GLYCERIN; HYDROXYACETOPHENONE; KAOLIN; POVIDONE K90; POLYSORBATE 80

84165-010 CHINESE RED TIGER LIDOCAINE PATCHES

ACTIVE INGREDIENT

LIDOCAINE 4%
MENTHOL 1%

PURPOSE

Topical anesthetic

INDICATIONS AND USAGE

Temporarily relieves muscle soreness and minor jointpains in the wrist, knees, back, neck, hips, shoulderselbows.

WARNINGS

For external use only

DO NOT USE

more than 1 patch on your body at a time or withother topical anesthetics at the same time
on wounds or damaged skin
with a heating pad or device
with other ointments, creams, sprays, or liniments
if you are allergic to any ingredients of this product

WHEN USING

use only as directed
avoid contact with the eyes, mucous membranes, orrashes
do not bandage tightly
dispose of used patch in manner that always keepsproduct away from children and pets. Used patchesstill contain the drug product that can produce seriousadverse effects if a child or pet chews or ingests this patch.

STOP USE

localized skin reactions occur, such as rash, itching,redness, irritation, pain, swelling and blistering
condition worsens
symptoms persist for more than 7 days
symptoms clear up and occur again within a fewdays

KEEP OUT OF REACH OF CHILDREN

If swallowed accidentally , get medical help orcontact with Poison Control Center immediately.

DOSAGE AND ADMINISTRATION

Adults and Children above 12 years old:
Clean and dry the affected area.
Tear off the protective film and apply the exposedpart of the patch to the affected area.
Carefully remove remaining film while pressingthe patch firmly on the skin.
Apply 1 patch at a time to affected area, not morethan 3 to 4 times daily.
Remove patch from the skin after at most 8-hour application
Children under age of 12:Consult a doctor

INACTIVE INGREDIENT

Dihydroxyaluminum Aminoacetate
Edetate Disodium
Glycerin
Hydroxyacetophenone
Kaolin
Mineral Oil
Polyacrylic Acid
Polysorbate 80
PolyvinylPyrrolidone
Propylene Glycol
Sodium Polyacrylate
Tartaric Acid
Titanium Dioxide
Water